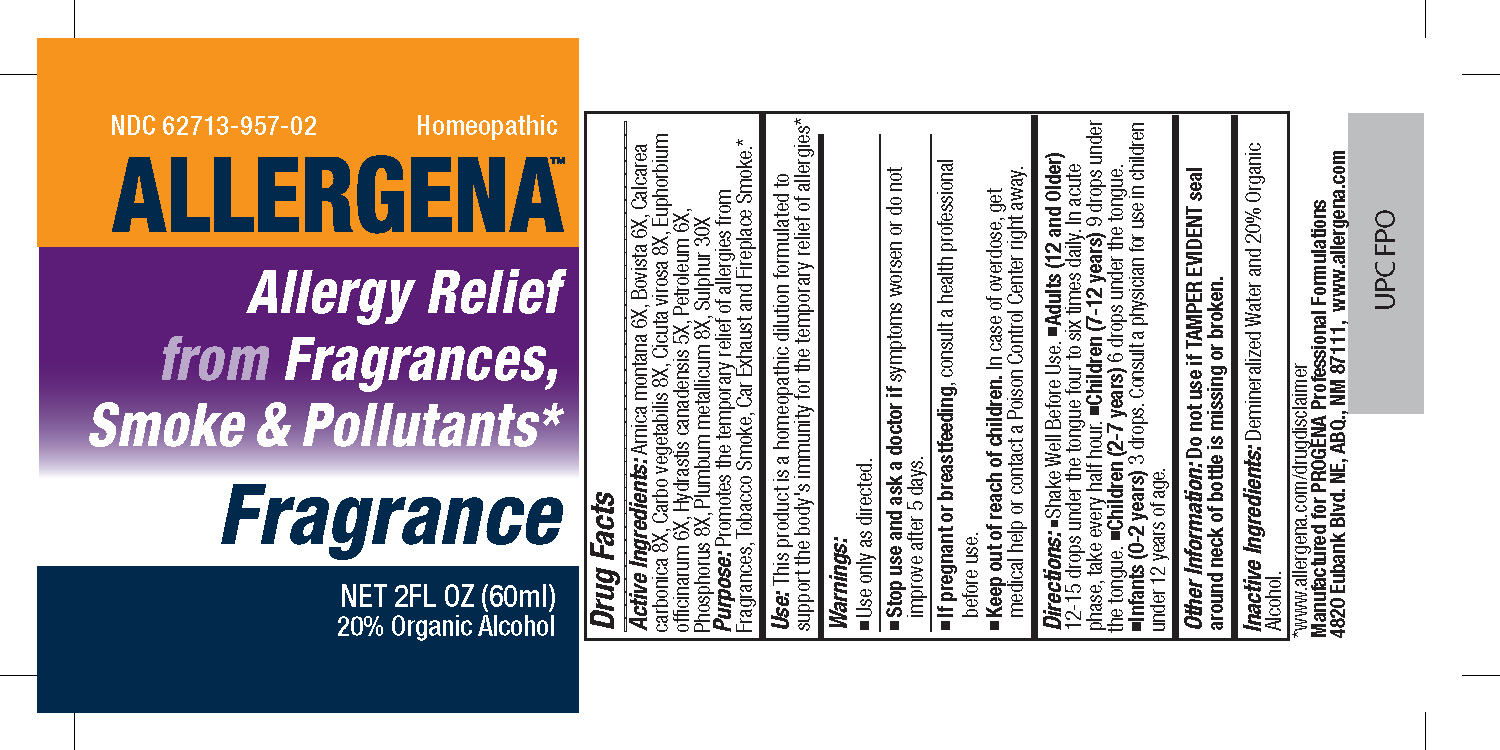 DRUG LABEL: Allergena Fragrance
NDC: 62713-957 | Form: LIQUID
Manufacturer: Meditrend, Inc. DBA Progena Professional Formulations
Category: homeopathic | Type: HUMAN OTC DRUG LABEL
Date: 20250128

ACTIVE INGREDIENTS: GOLDENSEAL 5 [hp_X]/1 mL; ARNICA MONTANA 6 [hp_X]/1 mL; LYCOPERDON UTRIFORME FRUITING BODY 6 [hp_X]/1 mL; CICUTA VIROSA ROOT 8 [hp_X]/1 mL; EUPHORBIA RESINIFERA RESIN 6 [hp_X]/1 mL; KEROSENE 6 [hp_X]/1 mL; OYSTER SHELL CALCIUM CARBONATE, CRUDE 8 [hp_X]/1 mL; ACTIVATED CHARCOAL 8 [hp_X]/1 mL; PHOSPHORUS 8 [hp_X]/1 mL; LEAD 8 [hp_X]/1 mL; SULFUR 30 [hp_X]/1 mL
INACTIVE INGREDIENTS: ALCOHOL; WATER

Allergena Fragrance

ACTIVE INGREDIENT

Active Ingredients: Arnica montana 6X, Bovista 6X, Calcerea carbonica 8X, Carbo vegetabilis 8X, Cicuta virosa 8X, Euphorbium officinarum 6X, Hydrastis canadensis 5X, Petroleum 6X, Phosphorus 8X, Plumbum metallicum 8X, Sulfur 30X

PURPOSE

Purpose:Promotes the temporary relief of allergies from Fragrances, Tobacco Smoke, Car Exhaust and Fireplace Smoke.*

Keep Out of Reach of Children.In case of overdose, get medical help or contact a
Poison Control Center right away.

INDICATIONS AND USAGE

Use: This product is a Homeopathic Dilution formulated to support the body's immunity for the temporary relief of allergies.*

Warnings:

- Use Only as directed.
- Stop use and ask a doctor if symptoms worsen or do not improve after 5 days.
- If pregnant or breast-feeding, consult a health professional before use.

DOSAGE AND ADMINISTRATION

Directions: • Shake Well Before Use. • Adults (12 and Older) 12-15 drops under the tongue four to six times daily. In acute phase, take every half hour. • Children (7-12 years)9 drops under the tongue. • Children (2-7 years)6 drops under the tongue. • Infants (0-2 years) 3 drops. Consult a physician for use in children under 12 years of age.

Other Information: Do not use if TAMPER EVIDENT seal around neck of bottle is missing or broken.

Inactive Ingredients: Demineralized Water and 20% USP Alcohol.

PACKAGE LABEL

*www.allergena.com/drugdisclaimer

Manufactured for Progena Professional Formulations

4820 Eubank Blvd. NE, ABQ, NM 87111, www.allergena.com